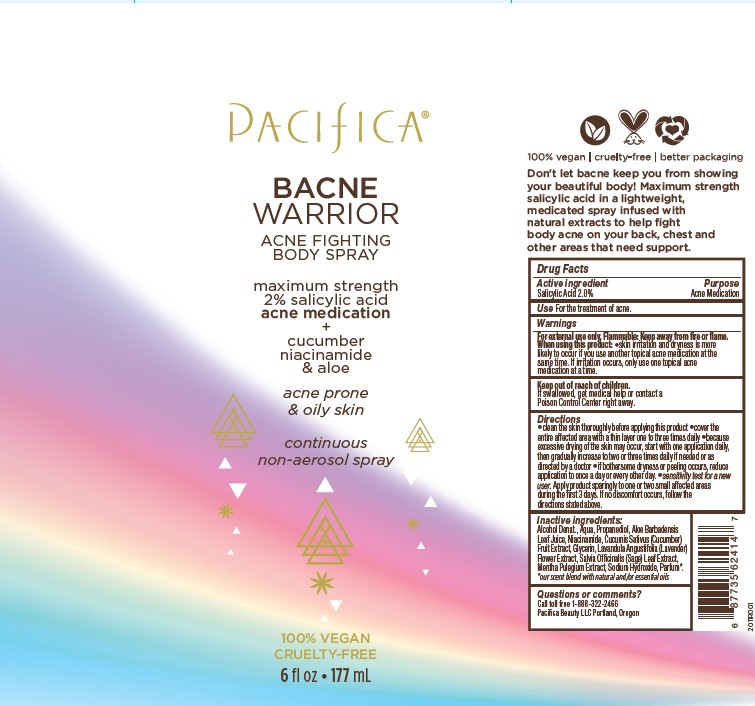 DRUG LABEL: Pacifica Bacne Warrior
NDC: 61197-103 | Form: SPRAY
Manufacturer: Pacifica Beauty, LLC
Category: otc | Type: HUMAN OTC DRUG LABEL
Date: 20250103

ACTIVE INGREDIENTS: SALICYLIC ACID 2 g/100 mg
INACTIVE INGREDIENTS: ALOE VERA LEAF; NIACINAMIDE; ALCOHOL; MENTHA PULEGIUM; WATER; LAVANDULA ANGUSTIFOLIA FLOWER; SAGE OIL; PROPANEDIOL; GLYCERIN; CUCUMIS SATIVUS WHOLE; SODIUM HYDROXIDE

Pacifica Bacne Warrior

Active ingredient Purpose

Salicylic Acid 2.0% Acne Medication

Use

For the treatment of acne.

Warnings

For external use only. Flammable: Keep away from fire or flame.

When using this product: skin irritation and dryness is more likely to occur if you use another topical acne medication at the same time. If irritation occurs, only use one topical acne medication at a time.

Keep out of reach of children.
If swallowed, get medical help or contact a Poison Control Center right away.

Directions

Clean the skin thoroughly before applying this product. Cover the entire affected area with a thin layer one to three times daily. Because excessive drying of the skin may occur, start with one application daily, then gradually increase to two or three times daily if needed or as directed by a doctor. If bothersome dryness or peeling occurs, reduce application to once a day or every other day. Sensitivity test for a new user. Apply product sparingly to one or two small affected areas during the first 3 days. If no discomfort occurs, follow the directions stated above.

Inactive ingredients:

Alcohol Denat., Aqua, Propanediol, Aloe Barbadensis Leaf Juice, Niacinamide, Cucumis Sativus (Cucumber) Fruit Extract, Glycerin, Lavandula Angustifolia (Lavender) Flower Extract, Salvia Officinalis (Sage) Leaf Extract, Mentha Pulegium Extract, Sodium Hydroxide, Parfum*. *our scent blend with natural and/or essential oils

Questions or comments?

Call toll free 1-888-322-2466
Pacifica Beauty LLC Portland, Oregon